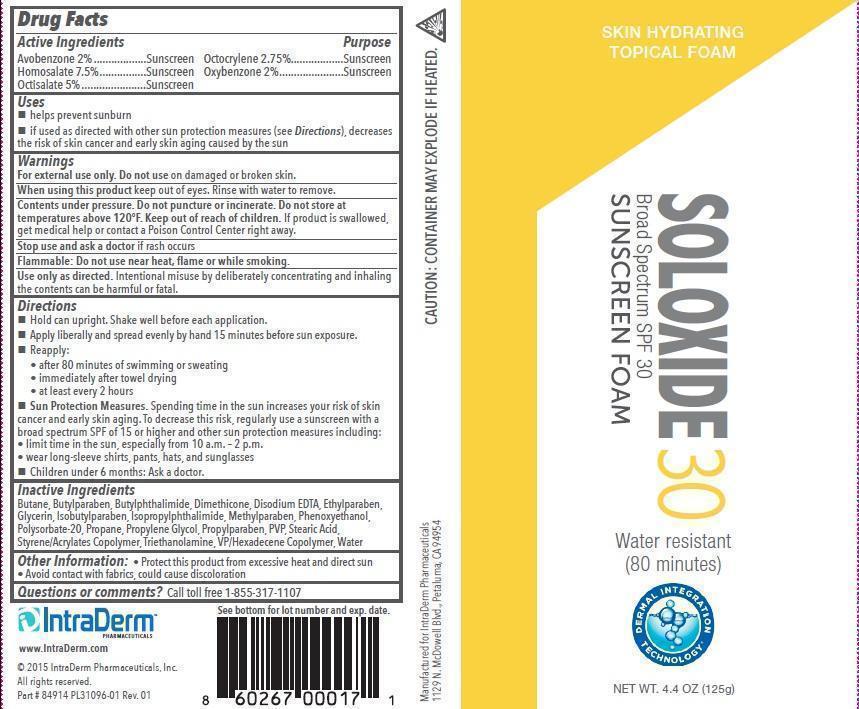 DRUG LABEL: Occulus
NDC: 13630-0089 | Form: AEROSOL
Manufacturer: Prime Packaging, Inc.
Category: otc | Type: HUMAN OTC DRUG LABEL
Date: 20200117

ACTIVE INGREDIENTS: AVOBENZONE 20 mg/1 g; HOMOSALATE 75 mg/1 g; OCTISALATE 50 mg/1 g; OCTOCRYLENE 275 mg/1 g; OXYBENZONE 20 mg/1 g
INACTIVE INGREDIENTS: N-BUTYLPHTHALIMIDE; ISOPROPYLPHTHALIMIDE; DIMETHICONE; EDETATE DISODIUM; GLYCERIN; PHENOXYETHANOL; METHYLPARABEN; ETHYLPARABEN; BUTYLPARABEN; PROPYLPARABEN; ISOBUTYLPARABEN; POLYSORBATE 20; PROPYLENE GLYCOL; POVIDONE, UNSPECIFIED; STEARIC ACID; ACRYLIC ACID; TROLAMINE; VINYLPYRROLIDONE/HEXADECENE COPOLYMER; WATER

Active ingredients

Avobenzone 2 %, Homosalate 7.5%, Octisalate 5 %, Octocrylene 2.75 %, and Oxybenzone 2 %

Purpose

Sunscreen

Uses

- helps prevent sunburn
- if used as directed with other sun protection measures (see Directions), decreases the risk of skin cancer and early skin aging caused by the sun

Warnings

OTHER SAFETY INFORMATION

For external use only. Do not use on damaged or broken skin.

When using this product keep out of eyes. Rinse with water to remove.

Stop use and ask a doctor if rash occurs

OTHER SAFETY INFORMATION

Flammable: Do not use near heat, flame or while smoking.

Directions

- Hold can upright. Shake well before each application.
- Apply liberally and spread evenly by hand 15 minutes before sun exposure
- Reapply:
- after 80 minutes of swimming or sweating
- immediately after towel drying
- at least every 2 hours
- Sun Protection Measures. Spending time in the sun increases your risk of skin cancer and early skin aging. To decrease this risk, regularly use a sunscreen with a broad spectrum SPF of 15 or higher and other sun protection measures including:
- limit time in the sun, especially from 10 a.m - 2 p.m.
- wear long-sleeve shirts, pants, hats, and sunglasses
- Children under 6 months: Ask a doctor.

Inactive Ingredients

Butane, Butylparaben, Butylphthalimide, Dimethicone,Disodium EDTA, Ethylparaben, Glycerin, Isobutylparaben, Isopropylphthalimide, Methylparaben, Phenoxyethanol, Polysorbate-20, Propane, Propylene Glycol, Propylparaben, PVP, Stearic Acid, Styrene/Acrylates Copolymer, Triethanolamine, VP/Hexadecene Copolymer, Water

PRINCIPAL DISPLAY PANEL - 125g Can Label

SKIN HYDRATING

TOPICAL FOAM

SOLOXIDE 30

Broad Spectrum SPF 30

SUNSCREEN FOAM

Water resistant

(80 minutes)

NET WT.4.4 OZ (125g)